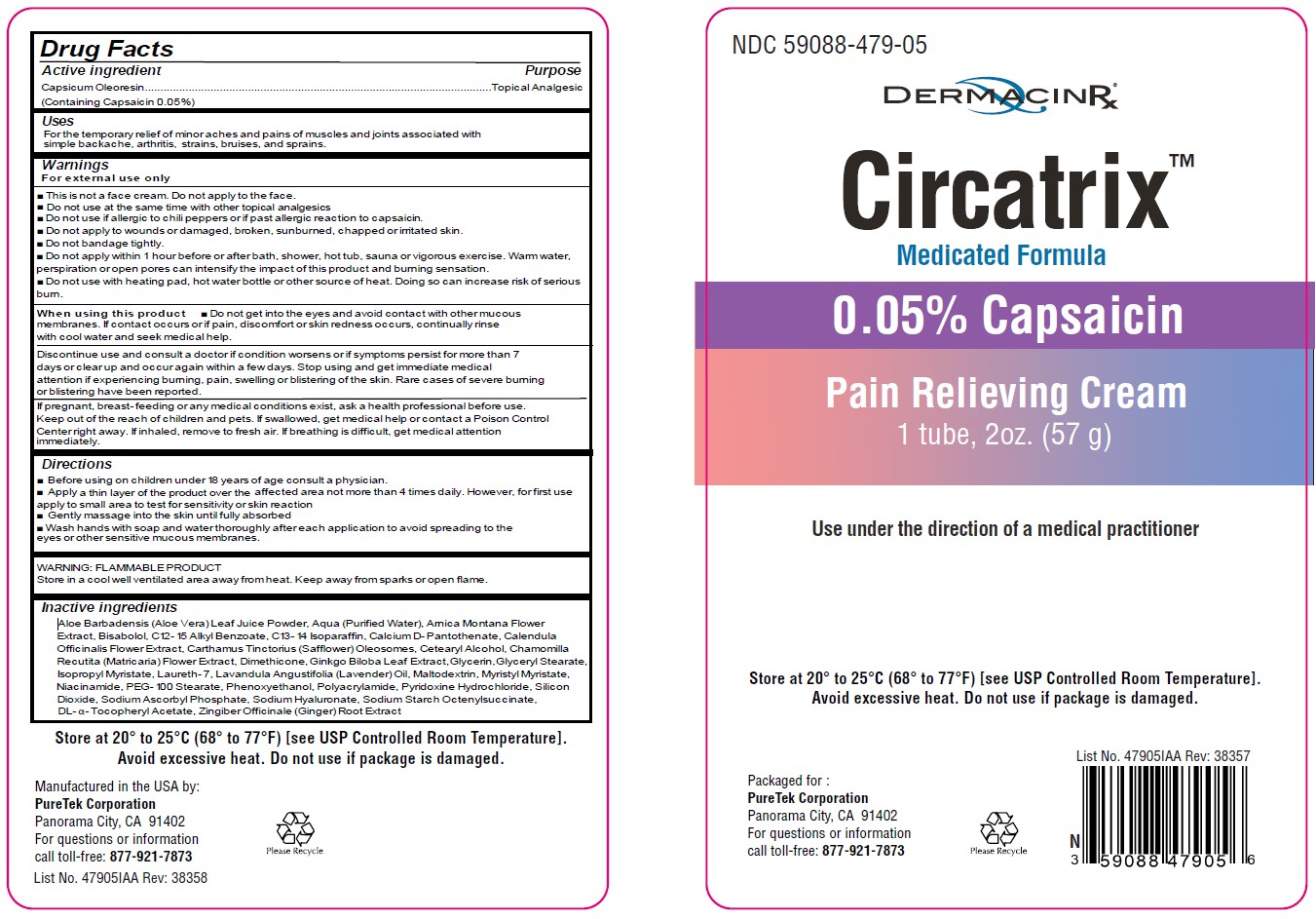 DRUG LABEL: Circatrix
NDC: 59088-479 | Form: CREAM
Manufacturer: PureTek Corporation
Category: otc | Type: HUMAN OTC DRUG LABEL
Date: 20241002

ACTIVE INGREDIENTS: CAPSICUM OLEORESIN 0.05 g/100 g
INACTIVE INGREDIENTS: POLYOXYL 100 STEARATE; WATER; ALOE VERA LEAF; ARNICA MONTANA FLOWER; GLYCERIN; PHENOXYETHANOL; LAURETH-7; CALCIUM PANTOTHENATE; CETOSTEARYL ALCOHOL; NIACINAMIDE; PYRIDOXINE HYDROCHLORIDE; CALENDULA OFFICINALIS FLOWER; CHAMOMILE; DIMETHICONE; .ALPHA.-TOCOPHEROL ACETATE, DL-; GINKGO; LAVENDER OIL; MALTODEXTRIN; ALKYL (C12-15) BENZOATE; MYRISTYL MYRISTATE; HYALURONATE SODIUM; OCTENYLSUCCINIC ACID; GLYCERYL MONOSTEARATE; GINGER; LEVOMENOL; C13-14 ISOPARAFFIN; CARTHAMUS TINCTORIUS (SAFFLOWER) OLEOSOMES; SODIUM ASCORBYL PHOSPHATE; ISOPROPYL MYRISTATE; POLYACRYLAMIDE (10000 MW); SILICON DIOXIDE

Circatrix™
0.05% Capsaicin
01-14-2022 - Edit marketing date from 03-01-2022 to 01-14-2022.

Active ingredient

Capsicum Oleoresin (Containing Capsaicin 0.05%)

Purpose

Topical Analgesic

Uses

For the temporary relief of minor aches and pains of muscles and joints associated with simple backache, arthritis, strains, bruises, and sprains.

Warnings

For external use only

DO NOT USE

- This is not a face cream. Do not apply to the face.
- Do not use at the same time with other topical analgesics
- Do not use if allergic to chili peppers or if past allergic reaction to capsaicin.
- Do not apply to wounds or damaged, broken, sunburned, chapped, or irritated skin.
- Do not bandage tightly.
- Do not apply within 1 hour before or after bath, shower, hot tub, sauna, or vigorous exercise. Warm water, perspiration, or open pores can intensify the impact of this product and burning sensation.
- Do not use with heating pad, hot water bottle or other source of heat. Doing so can increase risk of serious burn.

When using this product

- Do not get into the eyes and avoid contact with other mucous membranes. If contact occurs or if pain, discomfort, or skin redness occurs, continually rinse with cool water and seek medical help.

Discontinue use and consult a doctor if

condition worsens or if symptoms persist for more than 7 days or clear up and occur again within a few days. Stop using and get immediate medical attention if experience burning, pain, swelling, or blistering of the skin. Rare cases of severe burning or blistering have been reported.

If pregnant, breast- feeding or any medical conditions exist, ask a health professional before use.

Keep out of reach of children and pets.

If swallowed, get medical help or contact a Poison Control Center right away. If inhaled, remove to fresh air. If breathing is difficult, get medical attention immediately.

Directions

- Before using on children under 18 years of age consult a physician.
- Apply sparingly to affected area not more than 4 times daily. However, for first use, apply to small area to test for sensitivity or skin reaction
- Gently massage into the skin until fully absorbed
- Wash hands with soap and water thoroughly after each application to avoid spreading to the eyes or other sensitive mucous membranes.

Storage

WARNING: FLAMMABLE PRODUCT

Store in a cool well-ventilated area away from heat. Keep away from sparks or open flame.

Store at 20° to 25°C (68° to 77°F) [see USP Controlled Room Temperature]. Avoid excessive heat. Do not use if package is damaged.

Inactive ingredients

Aloe Barbadensis (Aloe Vera) Leaf Juice Powder, Aqua (Purified Water), Arnica Montana Flower Extract, Bisabolol, C12- 15 Alkyl Benzoate, C13- 14 Isoparaffin, Calcium D-Pantothenate, Calendula Officinalis Flower Extract, Carthamus Tinctorius (Safflower) Oleosomes, Cetearyl Alcohol, Chamomilla Recutita (Matricaria) Flower Extract, Dimethicone, DL- α- Tocopheryl Acetate, Ginkgo Biloba Leaf Extract, Glycerin, Glyceryl Stearate, Isopropyl Myristate, Laureth- 7, Lavandula Angustifolia (Lavender) Oil, Maltodextrin, Myristyl Myristate, Niacinamide, PEG- 100 Stearate, Phenoxyethanol, Polyacrylamide, Pyridoxine Hydrochloride, Silicon Dioxide, Sodium Ascorbyl Phosphate, Sodium Hyaluronate, Sodium Starch Octenylsuccinate, Zingiber Officinale (Ginger) Root Extract

Questions or comments?

For questions or information call toll-free: 877-921-7873

Circatrix™

Manufactured in the USA by:
PureTek Corporation
Panorama City, CA 91402
For questions or information
call toll-free: 877-921-7873